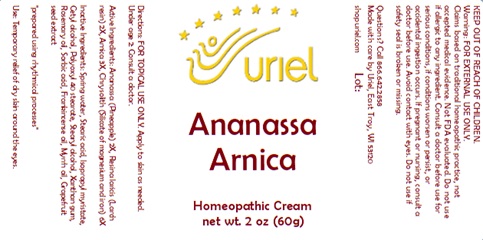 DRUG LABEL: Ananassa Arnica
NDC: 48951-1310 | Form: CREAM
Manufacturer: Uriel Pharmacy Inc.
Category: homeopathic | Type: HUMAN OTC DRUG LABEL
Date: 20240122

ACTIVE INGREDIENTS: LARIX DECIDUA RESIN 2 [hp_X]/1 g; PINEAPPLE 2 [hp_X]/1 g; ARNICA MONTANA FLOWER 3 [hp_X]/1 g; SILICON DIOXIDE 6 [hp_X]/1 g
INACTIVE INGREDIENTS: ROSEMARY OIL; XANTHAN GUM; MYRRH OIL; STEARIC ACID; ISOPROPYL MYRISTATE; POLYOXYL 40 STEARATE; STEARYL ALCOHOL; WATER; CETYL ALCOHOL; SORBIC ACID; FRANKINCENSE OIL; CITRUS PARADISI SEED

Ananassa Arnica

INDICATIONS AND USAGE

Directions: FOR TOPICAL USE ONLY.

DOSAGE AND ADMINISTRATION

Apply to skin as needed. Under age 2: Consult a doctor.

ACTIVE INGREDIENT

Active Ingredients: Ananassa (Pineapple) 2X, Resina laricis (Larch resin) 2X, Arnica 3X, Chrysolith (Silicate of magnesium and iron) 6X

INACTIVE INGREDIENT

Inactive Ingredients: Spring water, Stearic acid, Isopropyl myristate, Cetyl alcohol, Polyoxyl 40 stearate, Stearyl alcohol, Xanthan gum, Rosemary oil, Sorbic acid, Frankincense oil, Myrrh oil, Grapefruit seed extract

"prepared using rhythmical processes"

PURPOSE

Use: Temporary relief of dry skin around the eyes.

KEEP OUT OF REACH OF CHILDREN.

Questions? Call 866.642.2858
Made with care by Uriel, East Troy, WI 53120
shopuriel.com Lot:

WARNINGS

Warning: FOR EXTERNAL USE ONLY.
Claims based on traditional homeopathic practice, not accepted medical evidence. Not FDA evaluated. Do not use if allergic to any ingredient. Consult a doctor before use for serious conditions, if conditions worsen or persist, or accidental ingestion occurs. If pregnant or nursing, consult a doctor before use. Avoid contact with eyes. Do not use if safety seal is broken or missing.